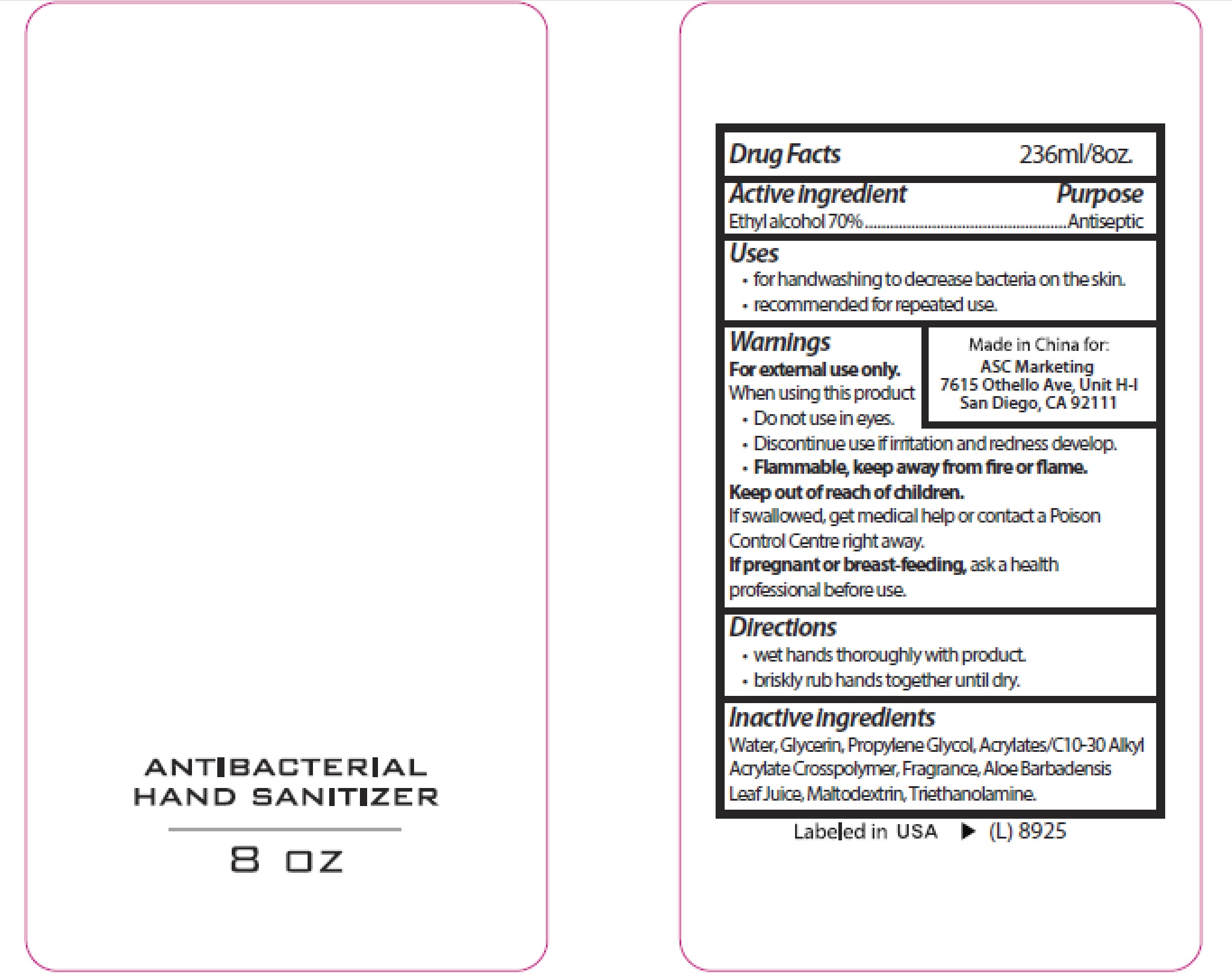 DRUG LABEL: ANTIBACTERIAL HAND SANITIZER
NDC: 73145-008 | Form: GEL
Manufacturer: ASC Marketing Ltd.
Category: otc | Type: HUMAN OTC DRUG LABEL
Date: 20201113

ACTIVE INGREDIENTS: ALCOHOL 70 mL/100 mL
INACTIVE INGREDIENTS: MALTODEXTRIN; CARBOMER COPOLYMER TYPE A (ALLYL PENTAERYTHRITOL CROSSLINKED); WATER; TROLAMINE; ALOE VERA LEAF; GLYCERIN; PROPYLENE GLYCOL

ASC ANTIBACTERIAL HAND SANITIZER

Active ingredient

Ethyl alcohol 70%

Purpose

Antiseptic

Uses

- for handwashing to decrease bacteria on the skin.
- recommended for repeated use.

Warnings

For external use only.

When using this product

- Do not use in eyes.
- Discontinue use if irritation and redness develop.
- Flammable, keep away from fire or flame.

Keep out of reach of children

If swallowed, get medical help or contact a Poison Control Centre right away.

If pregnant or breast-feeding, ask a health professional before use.

Directions

- wet hands thoroughly with product.
- briskly rub hands together until dry.

Inactive Ingredients

Water, Glycerin, Propylene Glycol, Acrylates/C10-30 Alkyl Acrylate Crosspolymer, Fragrance, Aloe Barbadensis Leaf Juice, Maltodextrin, Triethanolamine.